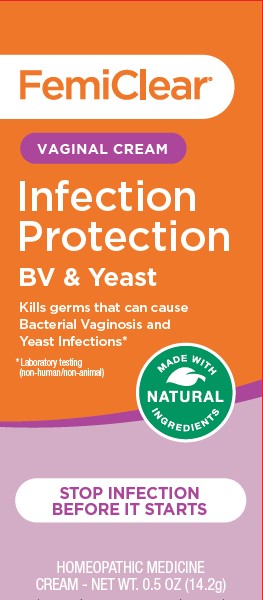 DRUG LABEL: FemiClear Infection Protection
NDC: 71042-028 | Form: CREAM
Manufacturer: OrganiCare Nature's Science, LLC
Category: homeopathic | Type: HUMAN OTC DRUG LABEL
Date: 20251020

ACTIVE INGREDIENTS: MELALEUCA CAJUPUTI WHOLE 0.01 g/1 g; THYMOL 0.01 g/1 g
INACTIVE INGREDIENTS: PENTYLENE GLYCOL; XANTHAN GUM; HYALURONIC ACID (NON-ANIMAL STABILIZED); CETYL ESTERS WAX; WATER

FemiClear Vaginal Cream

ACTIVE INGREDIENT

Melaleuca 6X HPUS ................................................... Anti-yeast agent
Olive Extract (Oleuropein) 5X HPUS..... Anti-microbial and healing agent
Thymol 6X HPUS .................................................. Anti-bacterial agent

INDICATIONS AND USAGE

This product is intended to help prevent bacterial vaginosis (BV) and
yeast infections, and to moisturize.

WARNINGS

For vaginal use only.
FemiClear may damage condoms and diaphragms and cause
them to fail.
FemiClear does not prevent sexually transmitted infections (STIs).
Practice safer sex by using a latex or polyurethane condom to
reduce the risk of getting STIs.
FemiClear does not eliminate the risk of infections.

DO NOT USE

if you are allergic to any ingredient in this product

WHEN USING

 can be used in combination with other medications, please consult a
healthcare professional
 do not use tampons, douches, spermicides or other vaginal products.
Condoms and diaphragms may be damaged and fail to prevent
pregnancy or sexually transmitted infections (STIs).

STOP USE

 rash or allergic reaction develops
 vaginal symptoms develop  you get a rash or hives, abdominal
pain, fever, chills, nausea or vomiting

PREGNANCY OR BREAST FEEDING

ask a healthcare professional before use.

ASK DOCTOR

 rash or allergic reaction develops
 vaginal symptoms develop  you get a rash or hives, abdominal
pain, fever, chills, nausea or vomiting

Directions
 Adults and children 12 years or over:
 Wash hands before and after use.
 Squeeze desired amount into applicator.
 Insert applicator into vagina and inject cream.
 Clean applicator after use and reuse.
 Children under 12 years: ask a doctor

 do not use if applicator wrapper is torn, open or incompletely sealed
 do not use if seal over tube opening has been punctured
 Store at 68° – 77° F (20° C – 25° C)

INACTIVE INGREDIENT

Water, Oxygenated Olive Oil, essential oil (natural fragrance), Cetearyl
Olivate, Sorbitan Olivate, Xanthan Gum, Cetyl Esters, Phenethyl Alcohol,
Pentylene Glycol, Hyaluronic Acid

QUESTIONS

Call 512.401.3572 or visit femiclear.com.

KEEP OUT OF REACH OF CHILDREN

Keep out of the reach of children. If swallowed, get medical
help or contact a Poison Control Center right away.

PURPOSE

This product is intended to help prevent bacterial vaginosis (BV) and
yeast infections, and to moisturize.